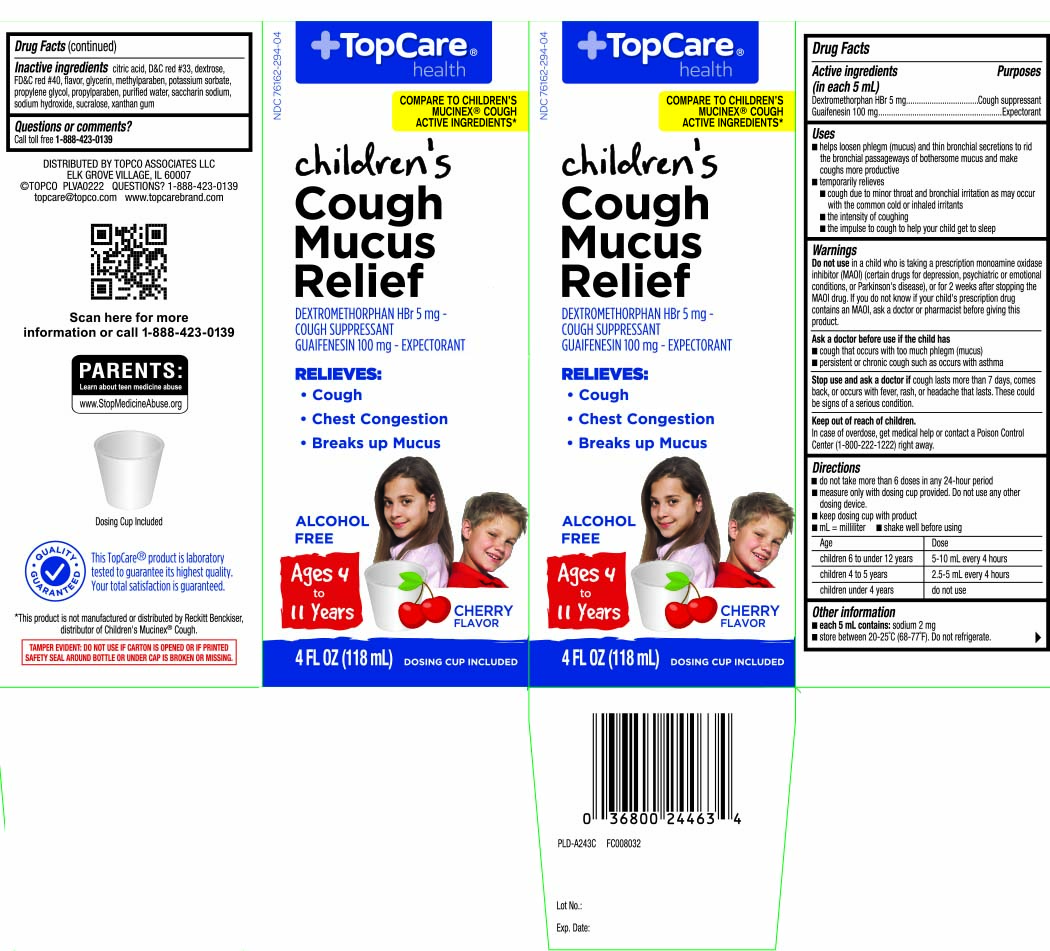 DRUG LABEL: Childrens Mucus Relief Cough
NDC: 76162-294 | Form: LIQUID
Manufacturer: Topco Associates
Category: otc | Type: HUMAN OTC DRUG LABEL
Date: 20251216

ACTIVE INGREDIENTS: DEXTROMETHORPHAN HYDROBROMIDE 5 mg/5 mL; GUAIFENESIN 100 mg/5 mL
INACTIVE INGREDIENTS: ANHYDROUS CITRIC ACID; D&C RED NO. 33; DEXTROSE; FD&C RED NO. 40; GLYCERIN; METHYLPARABEN; POTASSIUM SORBATE; PROPYLENE GLYCOL; PROPYLPARABEN; WATER; SACCHARIN SODIUM; SODIUM HYDROXIDE; SUCRALOSE; XANTHAN GUM

Drug Facts

Active ingredients (in each 5 mL)

Dextromethorphan HBr 5 mg

Guaifenesin 100 mg

Purposes

Cough suppressant

Expectorant

Uses

- helps loosen phlegm (mucus) and thin bronchial secretions to rid the bronchial passageways of bothersome mucus and make coughs more productive
- temporarily relieves:
  - cough due to minor throat and bronchial irritation as may occur with the common cold or inhaled irritants
  - the intensity of coughing
  - the impulse to cough to help your child get to sleep

Warnings

Do not use

in a child who is taking a prescription monoamine oxidase inhibitor (MAOI) (certain drugs for depression, psychiatric or emotional conditions, or Parkinson's disease), or for 2 weeks after stopping the MAOI drug. If you do not know if your child's prescription drug contains an MAOI, ask a doctor or pharmacist before taking this product.

Ask a doctor before use if the child has

- cough that occurs with too much phlegm (mucus)
- persistent or chronic cough such as occurs with asthma

Stop use and ask a doctor if

cough lasts more than 7 days, comes back, or occurs with fever, rash, or headache that lasts. These could be signs of a serious condition.

Keep out of reach of children.

In case of overdose, get medical help or contact a Poison Control Center (1-800-222-1222) right away.

Directions

- do not take more than 6 doses in any 24-hour period
- measure only with dosing cup provided. Do not use any other dosing device.
- keep dosing cup with product
- mL = milliliter
- shake well before using

age | dose
children 6 to under 12 years | 5-10 mL every 4 hours
children 4 to 5 years | 2.5-5 mL every 4 hours
children under 4 years | do not use

Other information

- each 5 mL contains: sodium 2 mg
- store between 20-25ºC (68-77º). Do not refrigerate.

Inactive ingredients

citric acid, D&C red #33, dextrose, FD&C red #40, flavor, glycerin, methylparaben, potassium sorbate, propylene glycol, propylparaben, purified water, saccharin sodium, sodium hydroxide, sucralose, xanthan gum

Questions or comments?

Call toll free 1-888-423-0139

Principal Display Panel

Compare to Children's Mucinex® Cough active ingredients*

Children's Cough Mucus Relief

Dextromethorphan HBr 5 mg - Cough Suppressant

Guaifenesin 100 mg - Expectorant

Relieves:

- cough
- chest congestion
- breaks up mucus

Alcohol Free

For Ages 4 to 11 Years

Cherry Flavor

FL OZ (mL)

Dosing Cup Included

*This product is not manufactured or distributed by Reckitt Benckiser, distributor of Children's Mucinex® Cough.

TAMPER EVIDENT: DO NOT USE IF CARTON IS OPENED OR IF PRINTED SAFETY SEAL AROUND BOTTLE OR UNDER CAP IS BROKEN OR MISSING.

Distributed by TOPCO ASSOCIATES LLC

ELK GROVE VILLAGE, IL 60007

topcare@topco.com www.topcarebrand.com

Package Label

Topcare Children's Mucus Relief Cough Cherry Liquid